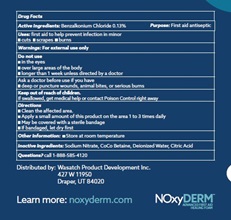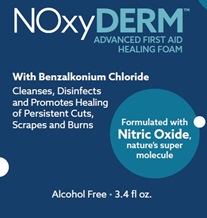 DRUG LABEL: NOxyDERM
NDC: 83823-001 | Form: LIQUID
Manufacturer: NOxy Health Products
Category: otc | Type: HUMAN OTC DRUG LABEL
Date: 20231127

ACTIVE INGREDIENTS: BENZALKONIUM CHLORIDE 0.13 g/100 mL
INACTIVE INGREDIENTS: COCO-BETAINE; ANHYDROUS CITRIC ACID; SODIUM NITRITE; WATER

Active Ingredient

Active Ingredient | Purpose
Benzalkonium Chloride 0.13% | First Aid Antiseptic

Purpose

First aid antiseptic

Uses: first aid to help prevent infection in minor:

- cuts
- scrapes
- burns

Do not use

- in the eyes
- over large areas of the body
- longer than 1 week unless directed by a doctor

Ask a doctor before use if you have

- deep or pucture wounds, animal bites, or serious burns

Warnings For external use only

Warnings

For external use only

Keep out of reach of children. If swallowed, get medical help or contact Poison Control right away

Instructions for use

Directions

- Clean the affected area
- Apply a small amount of this product on the area 1 to 3 times daily
- May be covered with a sterile bandage
- If bandaged, let dry first

Other safety information

Store at room temperature

Dosage

- Apply a small amount of this product on the area 1 to 3 times daily

Inactive ingredients

Sodium Nitrite

CoCo Betaine

Deionized Water

Citric Acid

Directions:

- Clean the affected area
- Apply a small amount of this product on the area 1 to 3 times daily
- May be covered with a sterile bandage
- If bandaged, let dry first

Warnings

For external use only

Questions

Questions? call 1-888-585-4120